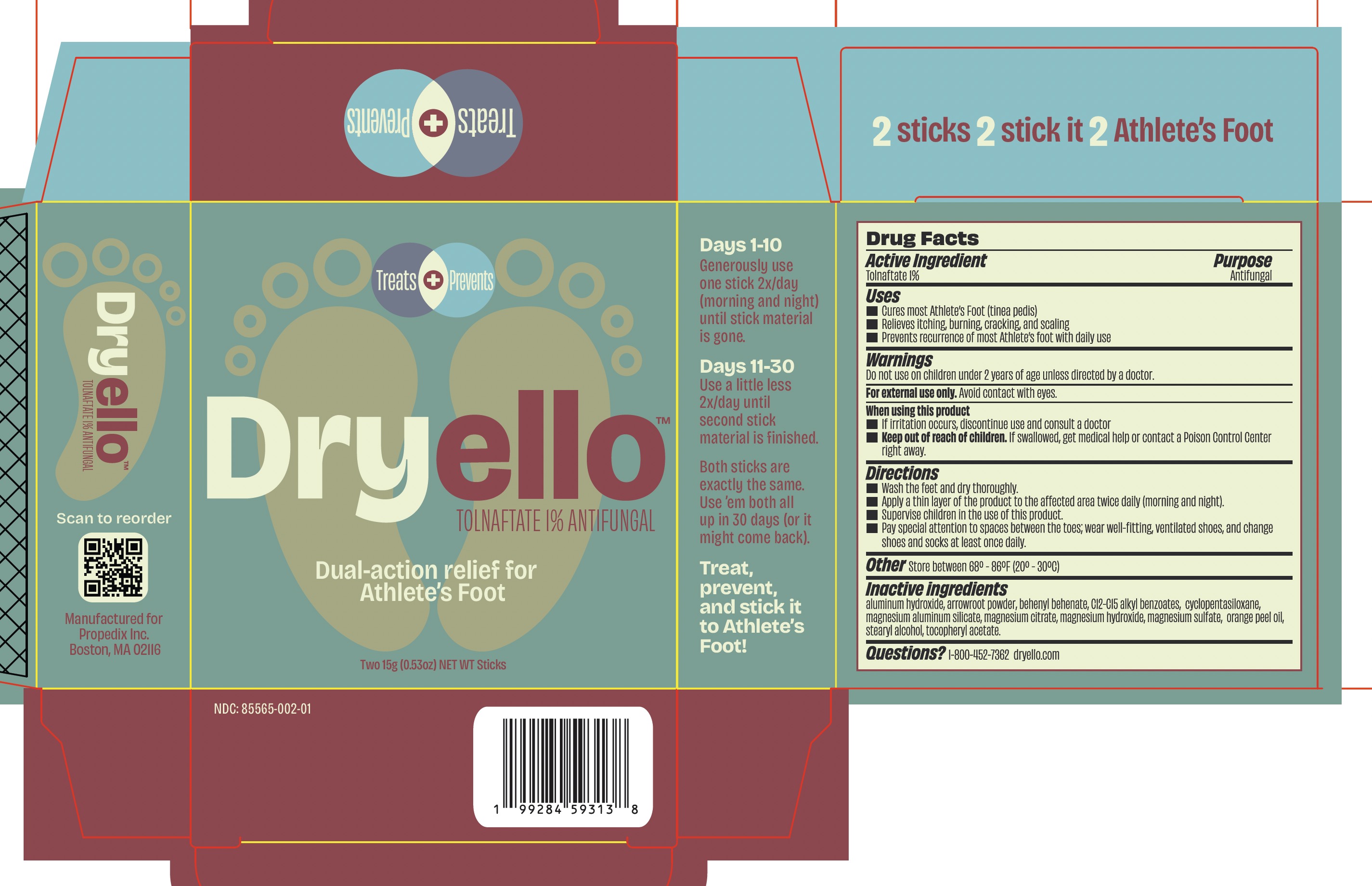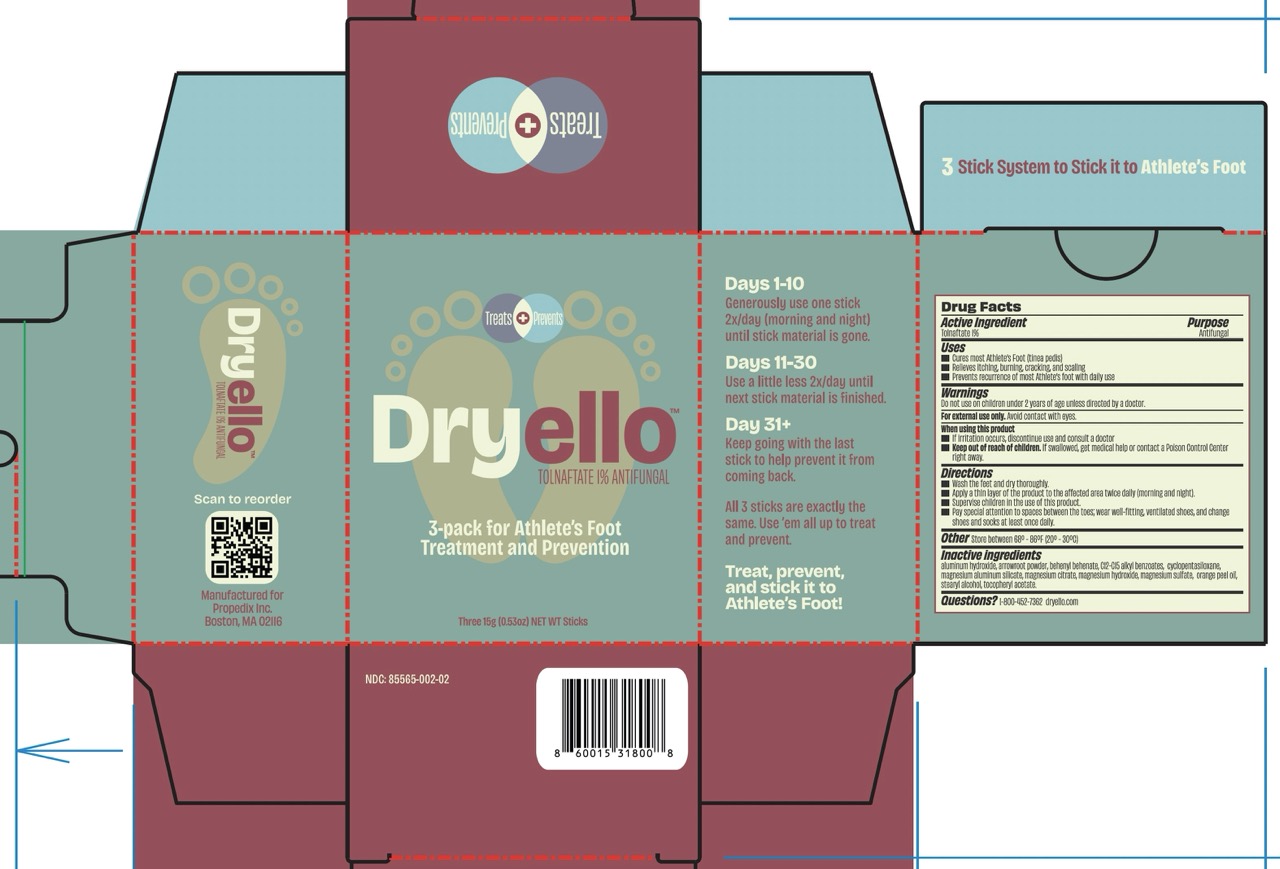 DRUG LABEL: Dryello Dual Action Relief for Athlete Foot
NDC: 85565-002 | Form: STICK
Manufacturer: ProPedix, Inc.
Category: otc | Type: HUMAN OTC DRUG LABEL
Date: 20260206

ACTIVE INGREDIENTS: TOLNAFTATE 1 g/100 g
INACTIVE INGREDIENTS: .ALPHA.-TOCOPHEROL ACETATE, DL-; C12-15 ALKYL BENZOATE; MAGNESIUM ALUMINUM SILICATE; MARANTA ARUNDINACEA ROOT; MAGNESIUM HYDROXIDE; MAGNESIUM CITRATE; BEHENYL BEHENATE; ORANGE OIL; CYCLOPENTASILOXANE; ALUMINUM HYDROXIDE; STEARYL ALCOHOL; MAGNESIUM SULFATE

Dryello Relief for Athlete's Foot - 0.53 oz Stick - 2pk, 3pk

Active Ingredient

Tolnaftate 1%

Purpose

Antifungal

Uses

- Cures most Athlete's Foot (tinea pedis)
- Relieves itching, burning, cracking, and scaling
- Prevents recurrence of most Athlete's foot with daily use

Warnings

Do not use on children under 2 years of age unless directed by a doctor.

For external use only. Avoid contact with eyes.

When using this product

- If irritation occurs, discontinue use and consult a doctor

Keep out of reach of children

If swallowed, get medical help or contact a Poison Control Center right away.

Directions

- Wash feet and dry thoroughly.
- Apply a think layer of the product to the affected area twice daily (morning and night).
- Supervise children in the use of this product.
- Pay special attention to spaces between toes; wear well-fitting, ventilated shoes, and change shoes and socks at least once daily.

Other

Store between 68º - 86ºF (20º - 30ºC)

Inactive ingredients

Aluminum Hydroxide, Arrowroot Powder, Behenyl Behenate, C12-15 Alkyl Benzoate, Cyclopentasiloxane, Magnesium Aluminum Silicate, Magnesium Citrate, Magnesium Hydroxide, Magnesium Sulfate, Orange Peel Oil, Stearyl Alcohol, Tocopheryl Acetate.

Questions?

1-800-452-7362 dryello.com

Principal Display Panel

Treats + Prevents

DryelloTM

TOLNAFTATE 1% ANTIFUNGAL

Dual-action relief for

Athlete's Foot

Two 15g (0.53oz) NET WT Sticks

Treats + Prevents

Dryello™

TOLNAFTATE 1% ANTIFUNGAL

3-pack for Athlete's Foot
Treatment and Prevention

Three 15g (0.53oz) NET WT Sticks